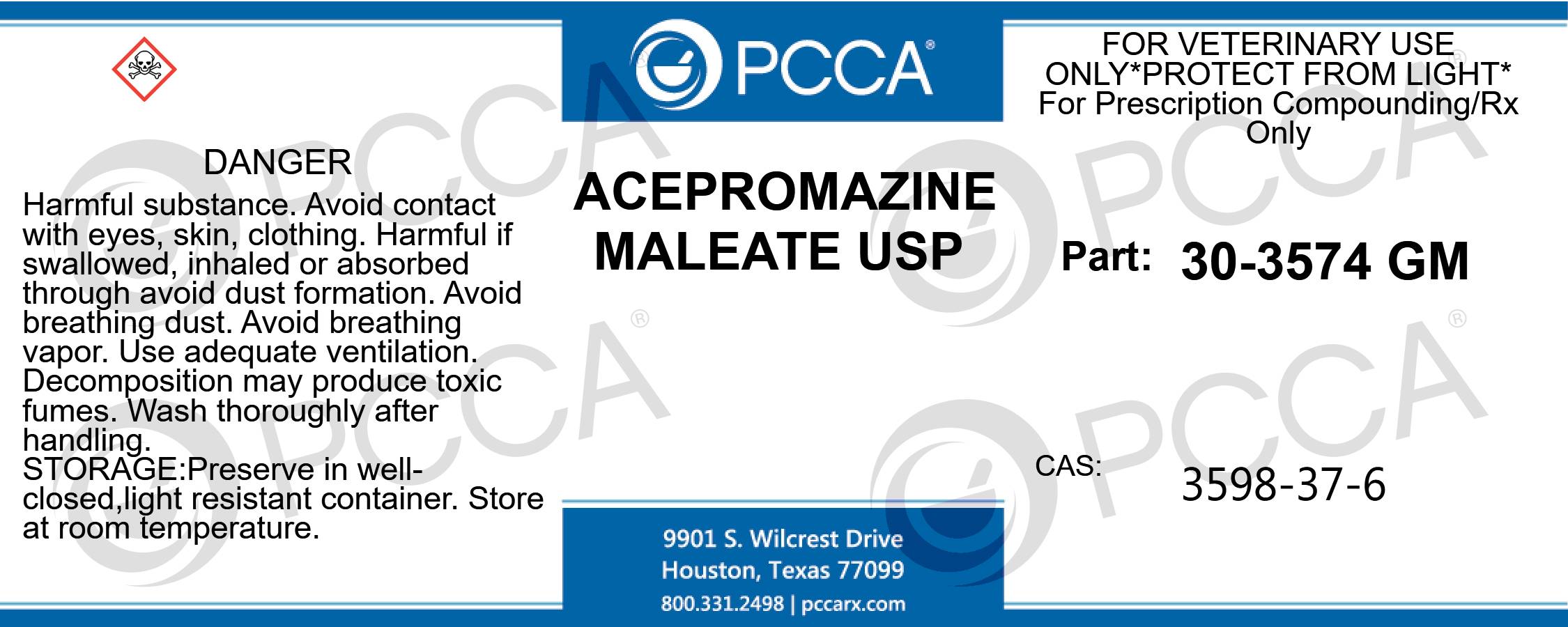 DRUG LABEL: Acepromazine Maleate
NDC: 51927-0259 | Form: POWDER
Manufacturer: Professional Compounding Centers of America
Category: other | Type: BULK INGREDIENT - ANIMAL DRUG
Date: 20221117

ACTIVE INGREDIENTS: ACEPROMAZINE MALEATE 25 kg/25 kg

30-3574 Acepromazine Maleate

ACEPROMAZINE MALEATE USP FOR VETERINARY USE ONLY *PROTECT FROM LIGHT* FOR PRESCRIPTION COMPOUNDING/NOT FOR FOOD ANIMALS PART: 30-3574 GM CAS: 3598-37-6 DANGER: HARMFUL SUBSTANCE. AVOID CONTACT WITH EYES, SKIN, CLOTHING. HARMFUL IF SWALLOWED, INHALED OR ABSORBED THROUGH AVOID DUST FORMATION. AVOID BREATHING DUST. AVOID BREATHING VAPOR. USE ADEQUATE VENTILATION. DECOMPOSITION MAY PRODUCE TOXIC FUMES. WASH THOROUGHLY AFTER HANDLING. PRESERVE IN WELL-CLOSED,LIGHT RESISTANT CONTAINER. STORE AT ROOM TEMPERATURE.

ACEPROMAZINE MALEATE USP
FOR VETERINARY USE ONLY *PROTECT FROM LIGHT*
FOR PRESCRIPTION COMPOUNDING/NOT FOR FOOD ANIMALS
PART: 30-3574 GM
CAS: 3598-37-6
DANGER: HARMFUL SUBSTANCE. AVOID CONTACT WITH EYES, SKIN, CLOTHING. HARMFUL IF SWALLOWED, INHALED OR ABSORBED THROUGH AVOID DUST FORMATION. AVOID BREATHING DUST. AVOID BREATHING VAPOR. USE ADEQUATE VENTILATION. DECOMPOSITION MAY PRODUCE TOXIC FUMES. WASH THOROUGHLY AFTER HANDLING. PRESERVE IN WELL-CLOSED,LIGHT RESISTANT CONTAINER. STORE AT ROOM TEMPERATURE.